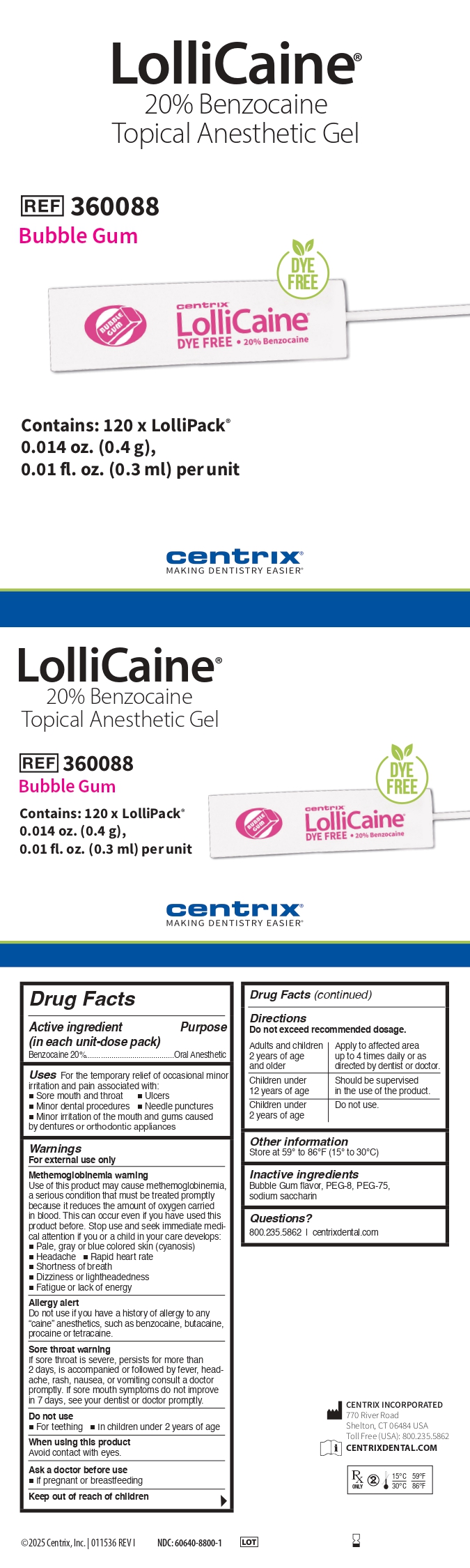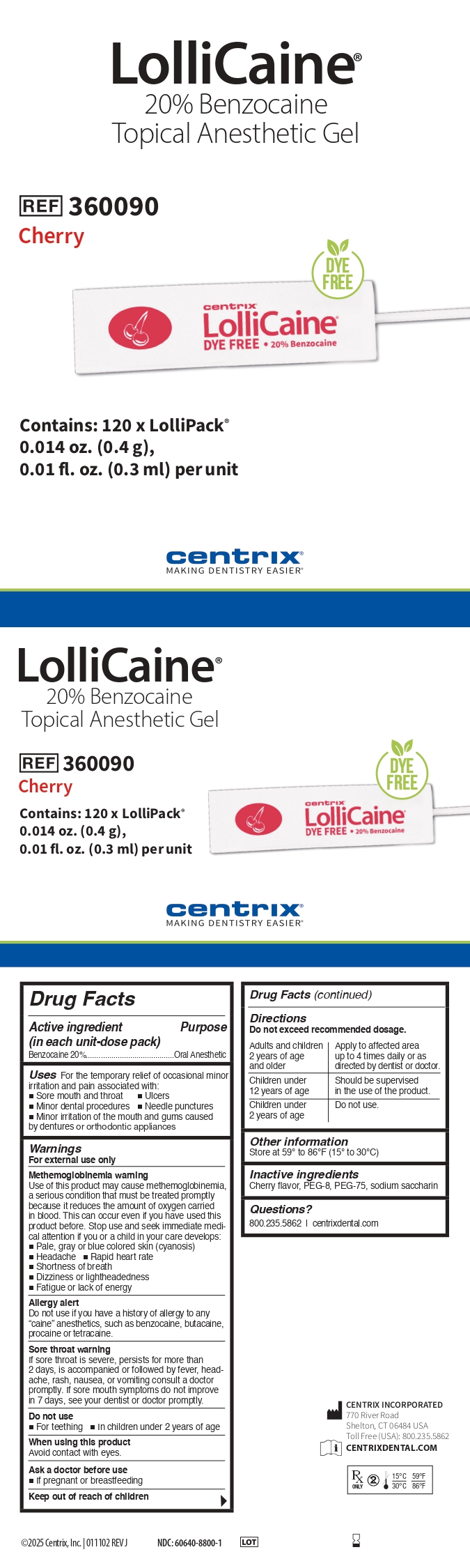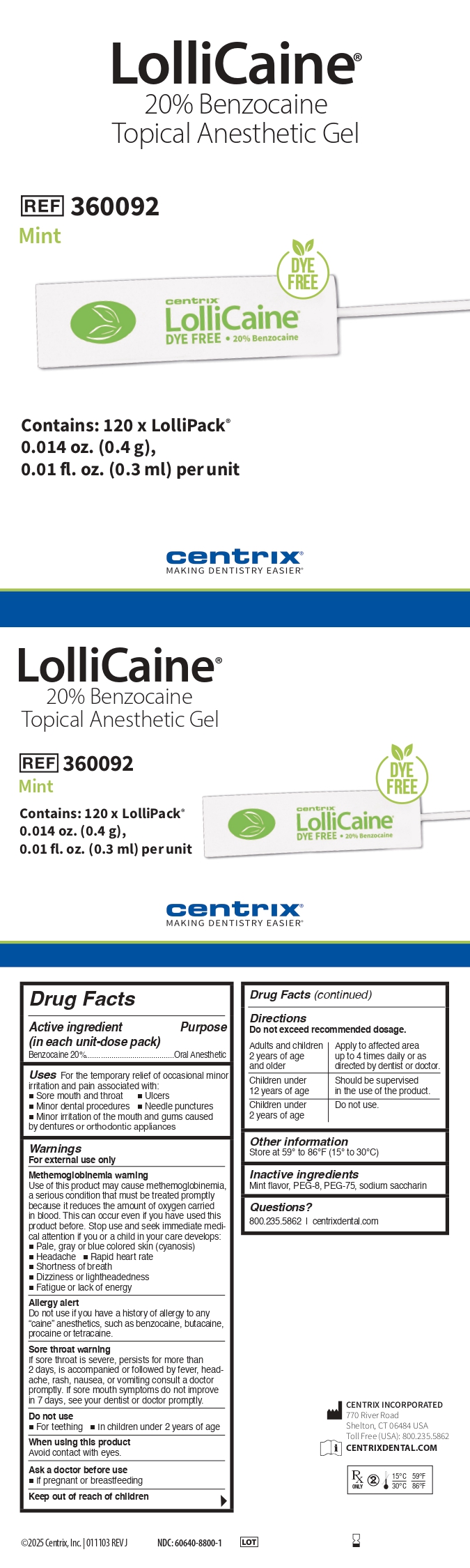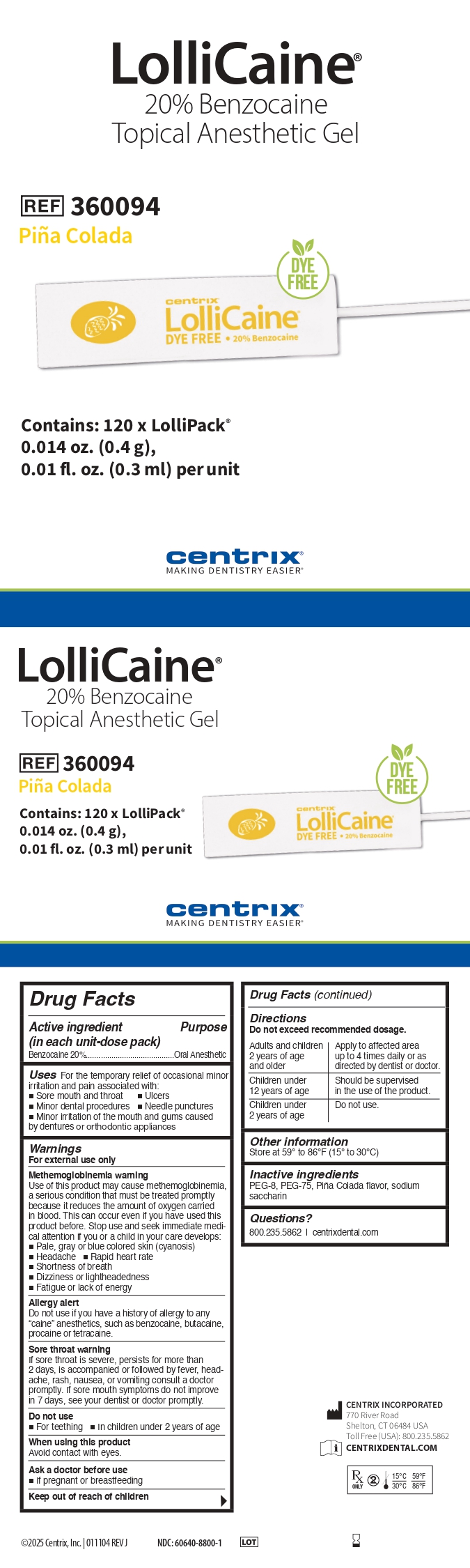 DRUG LABEL: LolliCaine Bubble Gum
NDC: 60640-8800 | Form: GEL, DENTIFRICE
Manufacturer: Centrix, Inc.
Category: otc | Type: HUMAN OTC DRUG LABEL
Date: 20251024

ACTIVE INGREDIENTS: BENZOCAINE 200 mg/1 g
INACTIVE INGREDIENTS: PEG-8; PEG-75; SACCHARIN SODIUM

Lollicaine Topical Anesthetic Gel/Liquid –
20% Benzocaine

Active ingredients

Benzocaine 20%

Purpose

Oral Anesthetic

Use

For the temporary relief of occasional minor irritation and pain, associated with:

- Sore mouth and throat
- Ulcers
- Minor dental procedures
- Needle punctures
- Minor irritation of the mouth and gums caused by dentures or orthodontic appliances

Warnings

For external use only

Methemoglobinemia Warning

Use of this product may cause methemoglobinemia, a serious condition that must be treated promptly because it reduces the amount of oxygen carried in blood. This can occur even if you have used this product before. Stop use and seek immediate medical attention if you or a child in your care develops:

- Pale, gray or blue colored skin (cyanosis)
- Headache
- Rapid heart rate
- Shortness of breath
- Dizziness or lightheadedness
- Fatigue or lack of energy

Allergy alert:

Do not use if you have a history of allergy to any “caine” anesthetics, such as benzocaine, butacaine, procaine or tetracaine.

Sore Throat Warning:

If sore throat is severe, persists for more than 2 days, is accompanied or followed by fever, headache, rash, nausea, or vomiting consult a doctor promptly. If sore mouth symptoms do not improve in 7 days, see your dentist or doctor promptly.

Do Not Use

- For teething
- In children under 2 years of age

When using this product

Avoid contact with eyes

Ask a doctor before use

- If pregnant or breastfeeding

Directions

Do not exceed recommended dosage.

Adults and children 2 years of age and older: Apply to affected area up to 4 times daily or as directed by dentist or doctor.

Children under 12 years of age: Should be supervised in the use of the product.

Children under 2 years of age: Do not use

Other information

Store at 59° to 86º F (15º to 30º C)

Questions or comments?

800.235.5862 | centrixdental.com

CENTRIX INCORPORATED
770 River Road
Shelton, CT 06484 USA
Toll Free (USA): 800.235.5862
CENTRIXDENTAL.COM

Inactive ingredients

Bubble Gum flavor contains:PEG-8, PEG-75, sodium saccharin

Cherry flavor contains:Cherry flavor, PEG-8, PEG-75, sodium saccharin

Mint flavor contains: Mint flavor, PEG-8, PEG-75, sodium saccharin

Pina Colada flavor contains:PEG-8, PEG-75, PinaColada flavor, sodium saccharin